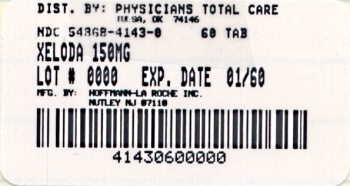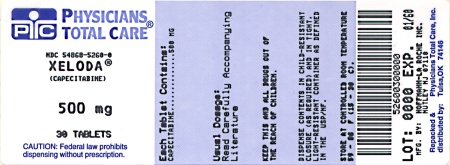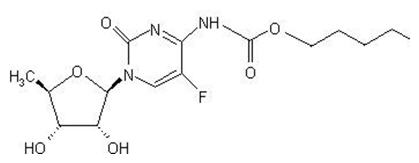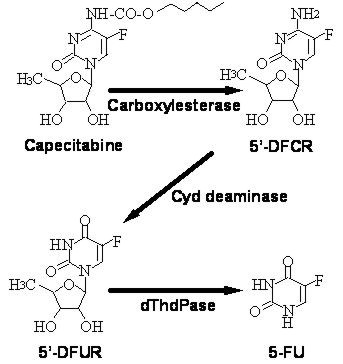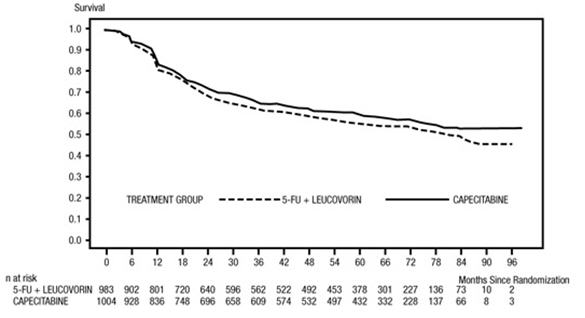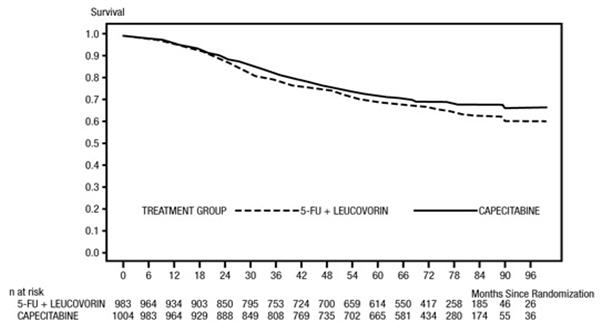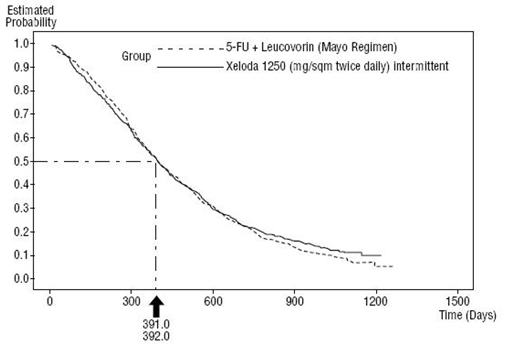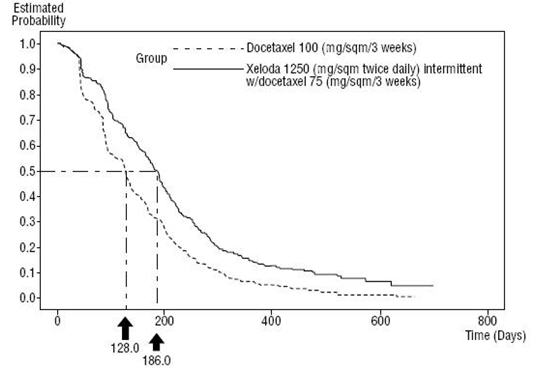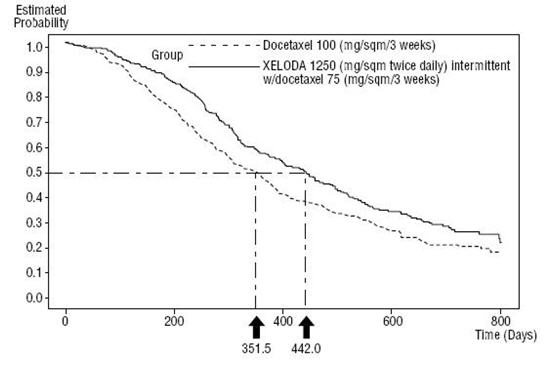 DRUG LABEL: Xeloda
NDC: 54868-4143 | Form: TABLET, FILM COATED
Manufacturer: Physicians Total Care, Inc.
Category: prescription | Type: HUMAN PRESCRIPTION DRUG LABEL
Date: 20120607

ACTIVE INGREDIENTS: capecitabine 150 mg/1 1
INACTIVE INGREDIENTS: croscarmellose sodium; hypromellose 2208 (15000 MPA.S); cellulose, microcrystalline; magnesium stearate; water; talc; titanium dioxide; FERRIC OXIDE RED; FERRIC OXIDE YELLOW

HIGHLIGHTS OF PRESCRIBING INFORMATION

These highlights do not include all the information needed to use XELODA® safely and effectively. See full prescribing information for XELODA®.
XELODA® (capecitabine) Tablets, Film Coated for Oral use
Initial U.S. Approval: 1998

WARNING: XELODA-WARFARIN INTERACTION

See full prescribing information for complete boxed warning.

Patients receiving concomitant XELODA and oral coumarin-derivative anticoagulants such as warfarin and phenprocoumon should have their anticoagulant response (INR or prothrombin time) monitored frequently in order to adjust the anticoagulant dose accordingly. Altered coagulation parameters and/or bleeding, including death, have been reported during concomitant use.

- Occurrence: Within several days and up to several months after initiating XELODA therapy; may also be seen within 1 month after stopping XELODA
- Predisposing factors: age>60 and diagnosis of cancer

1 INDICATIONS AND USAGE

XELODA (capecitabine) is a nucleoside metabolic inhibitor with antineoplastic activity indicated for:

- Adjuvant Colon Cancer (1.1)
  - Patients with Dukes' C colon cancer
- Metastatic Colorectal Cancer (1.1)
  - First-line as monotherapy when treatment with fluoropyrimidine therapy alone is preferred
- Metastatic Breast Cancer (1.2)
  - In combination with docetaxel after failure of prior anthracycline-containing therapy
  - As monotherapy in patients resistant to both paclitaxel and an anthracycline-containing regimen

2 DOSAGE AND ADMINISTRATION

- Take XELODA with water within 30 min after a meal (2)
- Monotherapy: 1250 mg/m^2 twice daily orally for 2 weeks followed by a one week rest period in 3-week cycles (2.1)
- Adjuvant treatment is recommended for a total of 6 months (8 cycles) (2.1)
- In combination with docetaxel, the recommended dose of XELODA is 1250 mg/m^2 twice daily for 2 weeks followed by a 7-day rest period, combined with docetaxel at 75 mg/m^2 as a 1-hour IV infusion every 3 weeks (2.1)
- XELODA dosage may need to be individualized to optimize patient management (2.2)
- Reduce the dose of XELODA by 25% in patients with moderate renal impairment (2.3)

3 DOSAGE FORMS AND STRENGTHS

- Tablets: 150 mg and 500 mg (3)

4 CONTRAINDICATIONS

- Dihydropyrimidine dehydrogenase (DPD) deficiency (4.1)
- Severe Renal Impairment (4.2)
- Hypersensitivity (4.3)

5 WARNINGS AND PRECAUTIONS

- Diarrhea: May be severe. Interrupt XELODA treatment immediately until diarrhea resolves or decreases to grade 1. Recommend standard antidiarrheal treatments. (5.1)
- Coagulopathy: May result in bleeding, death. Monitor anticoagulant response (e.g., INR) and adjust anticoagulant dose accordingly. (5.2)
- Cardiotoxicity: Common in patients with a prior history of coronary artery disease. (5.3)
- Pregnancy: Can cause fetal harm. Advise women of the potential risk to the fetus. (5.6, 8.1)
- Hand-and-Foot Syndrome (Grade 2 or 3): Interrupt XELODA treatment until the event resolves or decreases in intensity. (5.7)
- Hyperbilirubinemia (Grade 2 to 4): Interrupt XELODA treatment immediately until the hyperbilirubinemia resolves or decreases in intensity. (5.8)
- Hematologic: Do not treat patients with neutrophil counts <1.5 × 10^9/L or thrombocyte counts <100 × 10^9/L. If grade 3-4 neutropenia or thrombocytopenia occurs, stop therapy until condition resolves. (5.9)

6 ADVERSE REACTIONS

Most common adverse reactions (≥30%) were diarrhea, hand-and-foot syndrome, nausea, vomiting, abdominal pain, fatigue/weakness, and hyperbilirubinemia. Other adverse reactions, including serious adverse reactions, have been reported. (6)

To report SUSPECTED ADVERSE REACTIONS, contact Genentech at 1-888-835-2555 or FDA at 1-800-FDA-1088 or www.fda.gov/medwatch

7 DRUG INTERACTIONS

- Anticoagulants: Monitor anticoagulant response (INR or prothrombin time) frequently in order to adjust the anticoagulant dose as needed. (5.2, 7.1)
- Phenytoin: Monitor phenytoin levels in patients taking XELODA concomitantly with phenytoin. The phenytoin dose may need to be reduced. (7.1)
- Leucovorin: The concentration of 5-fluorouracil is increased and its toxicity may be enhanced by leucovorin. (7.1)
- CYP2C9 substrates: Care should be exercised when XELODA is coadministered with CYP2C9 substrates. (7.1)
- Food reduced both the rate and extent of absorption of capecitabine. (2, 7.1, 12.3)

8 USE IN SPECIFIC POPULATIONS

- Nursing Mothers: Discontinue nursing when receiving XELODA treatment. (8.3)
- Geriatric: Greater incidence of adverse reactions. Monitoring required. (8.5)
- Hepatic Impairment: Monitoring is recommended in patients with mild to moderate hepatic impairment. (8.6)
- Renal Impairment: Reduce XELODA starting dose in patients with moderate renal impairment (2.3, 8.7, 12.3)

FULL PRESCRIBING INFORMATION

WARNING: XELODA-WARFARIN INTERACTION

XELODA Warfarin Interaction: Patients receiving concomitant capecitabine and oral coumarin-derivative anticoagulant therapy should have their anticoagulant response (INR or prothrombin time) monitored frequently in order to adjust the anticoagulant dose accordingly. A clinically important XELODA-Warfarin drug interaction was demonstrated in a clinical pharmacology trial [see Warnings and Precautions (5.2) and Drug Interactions (7.1)]. Altered coagulation parameters and/or bleeding, including death, have been reported in patients taking XELODA concomitantly with coumarin-derivative anticoagulants such as warfarin and phenprocoumon. Postmarketing reports have shown clinically significant increases in prothrombin time (PT) and INR in patients who were stabilized on anticoagulants at the time XELODA was introduced. These events occurred within several days and up to several months after initiating XELODA therapy and, in a few cases, within 1 month after stopping XELODA. These events occurred in patients with and without liver metastases. Age greater than 60 and a diagnosis of cancer independently predispose patients to an increased risk of coagulopathy.

1 INDICATIONS AND USAGE

1.1 Colorectal Cancer

- XELODA is indicated as a single agent for adjuvant treatment in patients with Dukes' C colon cancer who have undergone complete resection of the primary tumor when treatment with fluoropyrimidine therapy alone is preferred. XELODA was non-inferior to 5-fluorouracil and leucovorin (5-FU/LV) for disease-free survival (DFS). Physicians should consider results of combination chemotherapy trials, which have shown improvement in DFS and OS, when prescribing single-agent XELODA in the adjuvant treatment of Dukes' C colon cancer.
- XELODA is indicated as first-line treatment of patients with metastatic colorectal carcinoma when treatment with fluoropyrimidine therapy alone is preferred. Combination chemotherapy has shown a survival benefit compared to 5-FU/LV alone. A survival benefit over 5-FU/LV has not been demonstrated with XELODA monotherapy. Use of XELODA instead of 5-FU/LV in combinations has not been adequately studied to assure safety or preservation of the survival advantage.

1.2 Breast Cancer

- XELODA in combination with docetaxel is indicated for the treatment of patients with metastatic breast cancer after failure of prior anthracycline-containing chemotherapy.
- XELODA monotherapy is also indicated for the treatment of patients with metastatic breast cancer resistant to both paclitaxel and an anthracycline-containing chemotherapy regimen or resistant to paclitaxel and for whom further anthracycline therapy is not indicated (e.g., patients who have received cumulative doses of 400 mg/m^2 of doxorubicin or doxorubicin equivalents). Resistance is defined as progressive disease while on treatment, with or without an initial response, or relapse within 6 months of completing treatment with an anthracycline-containing adjuvant regimen.

2 DOSAGE AND ADMINISTRATION

XELODA tablets should be swallowed whole with water within 30 minutes after a meal. XELODA dose is calculated according to body surface area.

2.1 Standard Starting Dose

Monotherapy (Metastatic Colorectal Cancer, Adjuvant Colorectal Cancer, Metastatic Breast Cancer)

The recommended dose of XELODA is 1250 mg/m^2 administered orally twice daily (morning and evening; equivalent to 2500 mg/m^2 total daily dose) for 2 weeks followed by a 1-week rest period given as 3-week cycles (see Table 1).

Adjuvant treatment in patients with Dukes' C colon cancer is recommended for a total of 6 months [ie, XELODA 1250 mg/m^2 orally twice daily for 2 weeks followed by a 1-week rest period, given as 3-week cycles for a total of 8 cycles (24 weeks)].

Table 1 XELODA Dose Calculation According to Body Surface Area
Dose Level 1250 mg/m^2 Twice a Day |  | Number of Tablets to be Taken at Each Dose (Morning and Evening)
Surface Area (m^2) | Total Daily Dose (mg) | 150 mg | 500 mg
≤ 1.25 | 3000 | 0 | 3
1.26-1.37 | 3300 | 1 | 3
1.38-1.51 | 3600 | 2 | 3
1.52-1.65 | 4000 | 0 | 4
1.66-1.77 | 4300 | 1 | 4
1.78-1.91 | 4600 | 2 | 4
1.92-2.05 | 5000 | 0 | 5
2.06-2.17 | 5300 | 1 | 5
≥ 2.18 | 5600 | 2 | 5

In Combination With Docetaxel (Metastatic Breast Cancer)

In combination with docetaxel, the recommended dose of XELODA is 1250 mg/m^2 twice daily for 2 weeks followed by a 1-week rest period, combined with docetaxel at 75 mg/m^2 as a 1-hour intravenous infusion every 3 weeks. Pre-medication, according to the docetaxel labeling, should be started prior to docetaxel administration for patients receiving the XELODA plus docetaxel combination. Table 1 displays the total daily dose of XELODA by body surface area and the number of tablets to be taken at each dose.

2.2 Dose Management Guidelines

General

XELODA dosage may need to be individualized to optimize patient management. Patients should be carefully monitored for toxicity and doses of XELODA should be modified as necessary to accommodate individual patient tolerance to treatment [see Clinical Studies (14)]. Toxicity due to XELODA administration may be managed by symptomatic treatment, dose interruptions and adjustment of XELODA dose. Once the dose has been reduced, it should not be increased at a later time. Doses of XELODA omitted for toxicity are not replaced or restored; instead the patient should resume the planned treatment cycles.

The dose of phenytoin and the dose of coumarin-derivative anticoagulants may need to be reduced when either drug is administered concomitantly with XELODA [see Drug Interactions (7.1)].

Monotherapy (Metastatic Colorectal Cancer, Adjuvant Colorectal Cancer, Metastatic Breast Cancer)

XELODA dose modification scheme as described below (see Table 2) is recommended for the management of adverse reactions.

Table 2 Recommended Dose Modifications of XELODA
Toxicity NCIC Grades | During a Course of Therapy | Dose Adjustment for Next Treatment (% of starting dose)
Grade 1 | Maintain dose level | Maintain dose level
Grade 2
-1st appearance | Interrupt until resolved to grade 0-1 | 100%
-2nd appearance | Interrupt until resolved to grade 0-1 | 75%
-3rd appearance | Interrupt until resolved to grade 0-1 | 50%
-4th appearance | Discontinue treatment permanently | -
Grade 3
-1st appearance | Interrupt until resolved to grade 0-1 | 75%
-2nd appearance | Interrupt until resolved to grade 0-1 | 50%
-3rd appearance | Discontinue treatment permanently | -
Grade 4
-1st appearance | Discontinue permanently OR If physician deems it to be in the patient's best interest to continue, interrupt until resolved to grade 0-1 | 50%

In Combination With Docetaxel (Metastatic Breast Cancer)

Dose modifications of XELODA for toxicity should be made according to Table 2 above for XELODA. At the beginning of a treatment cycle, if a treatment delay is indicated for either XELODA or docetaxel, then administration of both agents should be delayed until the requirements for restarting both drugs are met.

The dose reduction schedule for docetaxel when used in combination with XELODA for the treatment of metastatic breast cancer is shown in Table 3.

Table 3 Docetaxel Dose Reduction Schedule in Combination with XELODA
Toxicity NCIC Grades | Grade 2 | Grade 3 | Grade 4
1st appearance | Delay treatment until resolved to grade 0-1; Resume treatment with original dose of 75 mg/m^2 docetaxel | Delay treatment until resolved to grade 0-1; Resume treatment at 55 mg/m2 of docetaxel. | Discontinue treatment with docetaxel
2nd appearance | Delay treatment until resolved to grade 0-1; Resume treatment at 55 mg/m^2 of docetaxel. | Discontinue treatment with docetaxel | -
3rd appearance | Discontinue treatment with docetaxel | - | -

2.3 Adjustment of Starting Dose in Special Populations

Renal Impairment

No adjustment to the starting dose of XELODA is recommended in patients with mild renal impairment (creatinine clearance = 51 to 80 mL/min [Cockroft and Gault, as shown below]). In patients with moderate renal impairment (baseline creatinine clearance = 30 to 50 mL/min), a dose reduction to 75% of the XELODA starting dose when used as monotherapy or in combination with docetaxel (from 1250 mg/m^2 to 950 mg/m^2 twice daily) is recommended [see Use in Specific Populations (8.7) and Clinical Pharmacology (12.3)]. Subsequent dose adjustment is recommended as outlined in Table 2 and Table 3 (depending on the regimen) if a patient develops a grade 2 to 4 adverse event [see Warnings and Precautions (5.5)]. The starting dose adjustment recommendations for patients with moderate renal impairment apply to both XELODA monotherapy and XELODA in combination use with docetaxel.

Cockroft and Gault Equation:

(140 - age [yrs]) (body wt [kg])

Creatinine clearance for males =

—————————————

(72) (serum creatinine [mg/dL])

Creatinine clearance for females = 0.85 × male value

Geriatrics

Physicians should exercise caution in monitoring the effects of XELODA in the elderly. Insufficient data are available to provide a dosage recommendation.

3 DOSAGE FORMS AND STRENGTHS

XELODA is supplied as biconvex, oblong film-coated tablets for oral administration. Each light peach-colored tablet contains 150 mg of capecitabine and each peach-colored tablet contains 500 mg of capecitabine.

4 CONTRAINDICATIONS

4.1 Dihydropyrimidine Dehydrogenase (DPD) Deficiency

XELODA is contraindicated in patients with known dihydropyrimidine dehydrogenase (DPD) deficiency.

4.2 Severe Renal Impairment

XELODA is contraindicated in patients with severe renal impairment (creatinine clearance below 30 mL/min [Cockroft and Gault]) [see Use in Specific Populations (8.7) and Clinical Pharmacology (12.3)].

4.3 Hypersensitivity

XELODA is contraindicated in patients with known hypersensitivity to capecitabine or to any of its components. XELODA is contraindicated in patients who have a known hypersensitivity to 5-fluorouracil.

5 WARNINGS AND PRECAUTIONS

General

Patients receiving therapy with XELODA should be monitored by a physician experienced in the use of cancer chemotherapeutic agents. Most adverse reactions are reversible and do not need to result in discontinuation, although doses may need to be withheld or reduced [see Dosage and Administration (2.2)].

5.1 Diarrhea

XELODA can induce diarrhea, sometimes severe. Patients with severe diarrhea should be carefully monitored and given fluid and electrolyte replacement if they become dehydrated. In 875 patients with either metastatic breast or colorectal cancer who received XELODA monotherapy, the median time to first occurrence of grade 2 to 4 diarrhea was 34 days (range from 1 to 369 days). The median duration of grade 3 to 4 diarrhea was 5 days. National Cancer Institute of Canada (NCIC) grade 2 diarrhea is defined as an increase of 4 to 6 stools/day or nocturnal stools, grade 3 diarrhea as an increase of 7 to 9 stools/day or incontinence and malabsorption, and grade 4 diarrhea as an increase of ≥10 stools/day or grossly bloody diarrhea or the need for parenteral support. If grade 2, 3 or 4 diarrhea occurs, administration of XELODA should be immediately interrupted until the diarrhea resolves or decreases in intensity to grade 1. Following a reoccurrence of grade 2 diarrhea or occurrence of any grade 3 or 4 diarrhea, subsequent doses of XELODA should be decreased [see Dosage and Administration (2.2)]. Standard antidiarrheal treatments (eg, loperamide) are recommended.

Necrotizing enterocolitis (typhlitis) has been reported.

5.2 Coagulopathy

Patients receiving concomitant capecitabine and oral coumarin-derivative anticoagulant therapy should have their anticoagulant response (INR or prothrombin time) monitored closely with great frequency and the anticoagulant dose should be adjusted accordingly [see Boxed Warning and Drug Interactions (7.1)].

5.3 Cardiotoxicity

The cardiotoxicity observed with XELODA includes myocardial infarction/ischemia, angina, dysrhythmias, cardiac arrest, cardiac failure, sudden death, electrocardiographic changes, and cardiomyopathy. These adverse reactions may be more common in patients with a prior history of coronary artery disease.

5.4 Dihydropyrimidine Dehydrogenase Deficiency

Rarely, unexpected, severe toxicity (eg, stomatitis, diarrhea, neutropenia and neurotoxicity) associated with 5-fluorouracil has been attributed to a deficiency of dihydropyrimidine dehydrogenase (DPD) activity. A link between decreased levels of DPD and increased, potentially fatal toxic effects of 5-fluorouracil therefore cannot be excluded.

5.5 Renal Insufficiency

Patients with moderate renal impairment at baseline require dose reduction [see Dosage and Administration (2.3)]. Patients with mild and moderate renal impairment at baseline should be carefully monitored for adverse reactions. Prompt interruption of therapy with subsequent dose adjustments is recommended if a patient develops a grade 2 to 4 adverse event as outlined in Table 2 [see Dosage and Administration (2.2), Use in Specific Populations (8.6), and Clinical Pharmacology (12.3)].

5.6 Pregnancy

XELODA may cause fetal harm when given to a pregnant woman. Capecitabine caused embryolethality and teratogenicity in mice and embryolethality in monkeys when administered during organogenesis. If this drug is used during pregnancy, or if a patient becomes pregnant while receiving XELODA, the patient should be apprised of the potential hazard to the fetus [see Use in Specific Populations (8.1)].

5.7 Hand-and-Foot Syndrome

Hand-and-foot syndrome (palmar-plantar erythrodysesthesia or chemotherapy-induced acral erythema) is a cutaneous toxicity. Median time to onset was 79 days (range from 11 to 360 days) with a severity range of grades 1 to 3 for patients receiving XELODA monotherapy in the metastatic setting. Grade 1 is characterized by any of the following: numbness, dysesthesia/paresthesia, tingling, painless swelling or erythema of the hands and/or feet and/or discomfort which does not disrupt normal activities. Grade 2 hand-and-foot syndrome is defined as painful erythema and swelling of the hands and/or feet and/or discomfort affecting the patient's activities of daily living. Grade 3 hand-and-foot syndrome is defined as moist desquamation, ulceration, blistering or severe pain of the hands and/or feet and/or severe discomfort that causes the patient to be unable to work or perform activities of daily living. If grade 2 or 3 hand-and-foot syndrome occurs, administration of XELODA should be interrupted until the event resolves or decreases in intensity to grade 1. Following grade 3 hand-and-foot syndrome, subsequent doses of XELODA should be decreased [see Dosage and Administration (2.2)].

5.8 Hyperbilirubinemia

In 875 patients with either metastatic breast or colorectal cancer who received at least one dose of XELODA 1250 mg/m^2 twice daily as monotherapy for 2 weeks followed by a 1-week rest period, grade 3 (1.5-3 × ULN) hyperbilirubinemia occurred in 15.2% (n=133) of patients and grade 4 (>3 × ULN) hyperbilirubinemia occurred in 3.9% (n=34) of patients. Of 566 patients who had hepatic metastases at baseline and 309 patients without hepatic metastases at baseline, grade 3 or 4 hyperbilirubinemia occurred in 22.8% and 12.3%, respectively. Of the 167 patients with grade 3 or 4 hyperbilirubinemia, 18.6% (n=31) also had postbaseline elevations (grades 1 to 4, without elevations at baseline) in alkaline phosphatase and 27.5% (n=46) had postbaseline elevations in transaminases at any time (not necessarily concurrent). The majority of these patients, 64.5% (n=20) and 71.7% (n=33), had liver metastases at baseline. In addition, 57.5% (n=96) and 35.3% (n=59) of the 167 patients had elevations (grades 1 to 4) at both prebaseline and postbaseline in alkaline phosphatase or transaminases, respectively. Only 7.8% (n=13) and 3.0% (n=5) had grade 3 or 4 elevations in alkaline phosphatase or transaminases.

In the 596 patients treated with XELODA as first-line therapy for metastatic colorectal cancer, the incidence of grade 3 or 4 hyperbilirubinemia was similar to the overall clinical trial safety database of XELODA monotherapy. The median time to onset for grade 3 or 4 hyperbilirubinemia in the colorectal cancer population was 64 days and median total bilirubin increased from 8 µm/L at baseline to 13 µm/L during treatment with XELODA. Of the 136 colorectal cancer patients with grade 3 or 4 hyperbilirubinemia, 49 patients had grade 3 or 4 hyperbilirubinemia as their last measured value, of which 46 had liver metastases at baseline.

In 251 patients with metastatic breast cancer who received a combination of XELODA and docetaxel, grade 3 (1.5 to 3 × ULN) hyperbilirubinemia occurred in 7% (n=17) and grade 4 (>3 × ULN) hyperbilirubinemia occurred in 2% (n=5).

If drug-related grade 3 to 4 elevations in bilirubin occur, administration of XELODA should be immediately interrupted until the hyperbilirubinemia decreases to ≤3.0 X ULN [see recommended dose modifications under Dosage and Administration (2.2)].

5.9 Hematologic

In 875 patients with either metastatic breast or colorectal cancer who received a dose of 1250 mg/m^2 administered twice daily as monotherapy for 2 weeks followed by a 1-week rest period, 3.2%, 1.7%, and 2.4% of patients had grade 3 or 4 neutropenia, thrombocytopenia or decreases in hemoglobin, respectively. In 251 patients with metastatic breast cancer who received a dose of XELODA in combination with docetaxel, 68% had grade 3 or 4 neutropenia, 2.8% had grade 3 or 4 thrombocytopenia, and 9.6% had grade 3 or 4 anemia.

Patients with baseline neutrophil counts of <1.5 × 10^9/L and/or thrombocyte counts of <100 × 10^9/L should not be treated with XELODA. If unscheduled laboratory assessments during a treatment cycle show grade 3 or 4 hematologic toxicity, treatment with XELODA should be interrupted.

5.10 Geriatric Patients

Patients ≥80 years old may experience a greater incidence of grade 3 or 4 adverse reactions. In 875 patients with either metastatic breast or colorectal cancer who received XELODA monotherapy, 62% of the 21 patients ≥80 years of age treated with XELODA experienced a treatment-related grade 3 or 4 adverse event: diarrhea in 6 (28.6%), nausea in 3 (14.3%), hand-and-foot syndrome in 3 (14.3%), and vomiting in 2 (9.5%) patients. Among the 10 patients 70 years of age and greater (no patients were >80 years of age) treated with XELODA in combination with docetaxel, 30% (3 out of 10) of patients experienced grade 3 or 4 diarrhea and stomatitis, and 40% (4 out of 10) experienced grade 3 hand-and-foot syndrome.

Among the 67 patients ≥60 years of age receiving XELODA in combination with docetaxel, the incidence of grade 3 or 4 treatment-related adverse reactions, treatment-related serious adverse reactions, withdrawals due to adverse reactions, treatment discontinuations due to adverse reactions and treatment discontinuations within the first two treatment cycles was higher than in the <60 years of age patient group.

In 995 patients receiving XELODA as adjuvant therapy for Dukes' C colon cancer after resection of the primary tumor, 41% of the 398 patients ≥65 years of age treated with XELODA experienced a treatment-related grade 3 or 4 adverse event: hand-and-foot syndrome in 75 (18.8%), diarrhea in 52 (13.1%), stomatitis in 12 (3.0%), neutropenia/granulocytopenia in 11 (2.8%), vomiting in 6 (1.5%), and nausea in 5 (1.3%) patients. In patients ≥65 years of age (all randomized population; capecitabine 188 patients, 5-FU/LV 208 patients) treated for Dukes' C colon cancer after resection of the primary tumor, the hazard ratios for disease-free survival and overall survival for XELODA compared to 5-FU/LV were 1.01 (95% C.I. 0.80 – 1.27) and 1.04 (95% C.I. 0.79 – 1.37), respectively.

5.11 Hepatic Insufficiency

Patients with mild to moderate hepatic dysfunction due to liver metastases should be carefully monitored when XELODA is administered. The effect of severe hepatic dysfunction on the disposition of XELODA is not known [see Use in Specific Populations (8.6) and Clinical Pharmacology (12.3)].

5.12 Combination With Other Drugs

Use of XELODA in combination with irinotecan has not been adequately studied.

6 ADVERSE REACTIONS

Because clinical trials are conducted under widely varying conditions, adverse reaction rates observed in the clinical trials of a drug cannot be directly compared to rates in the clinical trials of another drug and may not reflect the rates observed in practice.

6.1 Adjuvant Colon Cancer

Table 4 shows the adverse reactions occurring in ≥5% of patients from one phase 3 trial in patients with Dukes' C colon cancer who received at least one dose of study medication and had at least one safety assessment. A total of 995 patients were treated with 1250 mg/m^2 twice a day of XELODA administered for 2 weeks followed by a 1-week rest period, and 974 patients were administered 5-FU and leucovorin (20 mg/m^2 leucovorin IV followed by 425 mg/m^2 IV bolus 5-FU on days 1-5 every 28 days). The median duration of treatment was 164 days for capecitabine-treated patients and 145 days for 5-FU/LV-treated patients. A total of 112 (11%) and 73 (7%) capecitabine and 5-FU/LV-treated patients, respectively, discontinued treatment because of adverse reactions. A total of 18 deaths due to all causes occurred either on study or within 28 days of receiving study drug: 8 (0.8%) patients randomized to XELODA and 10 (1.0%) randomized to 5-FU/LV.

Table 5 shows grade 3/4 laboratory abnormalities occurring in ≥1% of patients from one phase 3 trial in patients with Dukes' C colon cancer who received at least one dose of study medication and had at least one safety assessment.

Table 4 Percent Incidence of Adverse Reactions Reported in ≥5% of Patients Treated With XELODA or 5-FU/LV for Colon Cancer in the Adjuvant Setting (Safety Population)
 | Adjuvant Treatment for Colon Cancer (N=1969)
 | XELODA (N=995) |  | 5-FU/LV (N=974)
Body System/ Adverse Event | All Grades | Grade 3/4 | All Grades | Grade 3/4
Gastrointestinal Disorders
Diarrhea | 47 | 12 | 65 | 14
Nausea | 34 | 2 | 47 | 2
Stomatitis | 22 | 2 | 60 | 14
Vomiting | 15 | 2 | 21 | 2
Abdominal Pain | 14 | 3 | 16 | 2
Constipation | 9 | - | 11 | <1
Upper Abdominal Pain | 7 | <1 | 7 | <1
Dyspepsia | 6 | <1 | 5 | -
Skin and Subcutaneous Tissue Disorders
Hand-and-Foot Syndrome | 60 | 17 | 9 | <1
Alopecia | 6 | - | 22 | <1
Rash | 7 | - | 8 | -
Erythema | 6 | 1 | 5 | <1
General Disorders and Administration Site Conditions
Fatigue | 16 | <1 | 16 | 1
Pyrexia | 7 | <1 | 9 | <1
Asthenia | 10 | <1 | 10 | 1
Lethargy | 10 | <1 | 9 | <1
Nervous System Disorders
Dizziness | 6 | <1 | 6 | -
Headache | 5 | <1 | 6 | <1
Dysgeusia | 6 | - | 9 | -
Metabolism and Nutrition Disorders
Anorexia | 9 | <1 | 11 | <1
Eye Disorders
Conjunctivitis | 5 | <1 | 6 | <1
Blood and Lymphatic System Disorders
Neutropenia | 2 | <1 | 8 | 5
Respiratory Thoracic and Mediastinal Disorders
Epistaxis | 2 | - | 5 | -

Table 5 Percent Incidence of Grade 3/4 Laboratory Abnormalities Reported in ≥1% of Patients Receiving XELODA Monotherapy for Adjuvant Treatment of Colon Cancer (Safety Population)
Adverse Event | XELODA (n=995) Grade 3/4 % | IV 5-FU/LV (n=974) Grade 3/4 %
Increased ALAT (SGPT) | 1.6 | 0.6
Increased calcium | 1.1 | 0.7
Decreased calcium | 2.3 | 2.2
Decreased hemoglobin | 1.0 | 1.2
Decreased lymphocytes | 13.0 | 13.0
Decreased neutrophils | 2.2 | 26.2
Decreased neutrophils/granulocytes | 2.4 | 26.4
Decreased platelets | 1.0 | 0.7
Increased bilirubin | 20 | 6.3

6.2 Metastatic Colorectal Cancer

Monotherapy

Table 6 shows the adverse reactions occurring in ≥5% of patients from pooling the two phase 3 trials in first line metastatic colorectal cancer. A total of 596 patients with metastatic colorectal cancer were treated with 1250 mg/m^2 twice a day of XELODA administered for 2 weeks followed by a 1-week rest period, and 593 patients were administered 5-FU and leucovorin in the Mayo regimen (20 mg/m^2 leucovorin IV followed by 425 mg/m^2 IV bolus 5-FU, on days 1-5, every 28 days). In the pooled colorectal database the median duration of treatment was 139 days for capecitabine-treated patients and 140 days for 5-FU/LV-treated patients. A total of 78 (13%) and 63 (11%) capecitabine and 5-FU/LV-treated patients, respectively, discontinued treatment because of adverse reactions/intercurrent illness. A total of 82 deaths due to all causes occurred either on study or within 28 days of receiving study drug: 50 (8.4%) patients randomized to XELODA and 32 (5.4%) randomized to 5-FU/LV.

Table 6 Pooled Phase 3 Colorectal Trials: Percent Incidence of Adverse Reactions in ≥5% of Patients
Adverse Event | XELODA (n=596) |  |  | 5-FU/LV (n=593)
 | Total % | Grade 3 % | Grade 4 % | Total % | Grade 3 % | Grade 4 %
Number of Patients With > One Adverse Event | 96 | 52 | 9 | 94 | 45 | 9
Body System/Adverse Event
GI
Diarrhea | 55 | 13 | 2 | 61 | 10 | 2
Nausea | 43 | 4 | – | 51 | 3 | <1
Vomiting | 27 | 4 | <1 | 30 | 4 | <1
Stomatitis | 25 | 2 | <1 | 62 | 14 | 1
Abdominal Pain | 35 | 9 | <1 | 31 | 5 | –
Gastrointestinal Motility Disorder | 10 | <1 | – | 7 | <1 | –
Constipation | 14 | 1 | <1 | 17 | 1 | –
Oral Discomfort | 10 | – | – | 10 | – | –
Upper GI Inflammatory Disorders | 8 | <1 | – | 10 | 1 | –
Gastrointestinal Hemorrhage | 6 | 1 | <1 | 3 | 1 | –
Ileus | 6 | 4 | 1 | 5 | 2 | 1
Skin and Subcutaneous
Hand-and-Foot Syndrome | 54 | 17 | NA | 6 | 1 | NA
Dermatitis | 27 | 1 | – | 26 | 1 | –
Skin Discoloration | 7 | <1 | – | 5 | – | –
Alopecia | 6 | – | – | 21 | <1 | –
General
Fatigue/Weakness | 42 | 4 | – | 46 | 4 | –
Pyrexia | 18 | 1 | – | 21 | 2 | –
Edema | 15 | 1 | – | 9 | 1 | –
Pain | 12 | 1 | – | 10 | 1 | –
Chest Pain | 6 | 1 | – | 6 | 1 | <1
Neurological
Peripheral Sensory Neuropathy | 10 | – | – | 4 | – | –
Headache | 10 | 1 | – | 7 | – | –
Dizziness | 8 | <1 | – | 8 | <1 | –
Insomnia | 7 | – | – | 7 | – | –
Taste Disturbance | 6 | 1 | – | 11 | <1 | 1
Metabolism
Appetite Decreased | 26 | 3 | <1 | 31 | 2 | <1
Dehydration | 7 | 2 | <1 | 8 | 3 | 1
Eye
Eye Irritation | 13 | – | – | 10 | <1 | –
Vision Abnormal | 5 | – | – | 2 | – | –
Respiratory
Dyspnea | 14 | 1 | – | 10 | <1 | 1
Cough | 7 | <1 | 1 | 8 | – | –
Pharyngeal Disorder | 5 | – | – | 5 | – | –
Epistaxis | 3 | <1 | – | 6 | – | –
Sore Throat | 2 | – | – | 6 | – | –
Musculoskeletal
Back Pain | 10 | 2 | – | 9 | <1 | –
Arthralgia | 8 | 1 | – | 6 | 1 | –
Vascular
Venous Thrombosis | 8 | 3 | <1 | 6 | 2 | –
Psychiatric
Mood Alteration | 5 | – | – | 6 | <1 | –
Depression | 5 | – | – | 4 | <1 | –
Infections
Viral | 5 | <1 | – | 5 | <1 | –
Blood and Lymphatic
Anemia | 80 | 2 | <1 | 79 | 1 | <1
Neutropenia | 13 | 1 | 2 | 46 | 8 | 13
Hepatobiliary
Hyperbilirubinemia | 48 | 18 | 5 | 17 | 3 | 3
– Not observed
NA = Not Applicable

6.3 Breast Cancer

In Combination with Docetaxel

The following data are shown for the combination study with XELODA and docetaxel in patients with metastatic breast cancer in Table 7 and Table 8. In the XELODA and docetaxel combination arm the treatment was XELODA administered orally 1250 mg/m^2 twice daily as intermittent therapy (2 weeks of treatment followed by 1 week without treatment) for at least 6 weeks and docetaxel administered as a 1-hour intravenous infusion at a dose of 75 mg/m^2 on the first day of each 3-week cycle for at least 6 weeks. In the monotherapy arm docetaxel was administered as a 1-hour intravenous infusion at a dose of 100 mg/m^2 on the first day of each 3-week cycle for at least 6 weeks. The mean duration of treatment was 129 days in the combination arm and 98 days in the monotherapy arm. A total of 66 patients (26%) in the combination arm and 49 (19%) in the monotherapy arm withdrew from the study because of adverse reactions. The percentage of patients requiring dose reductions due to adverse reactions was 65% in the combination arm and 36% in the monotherapy arm. The percentage of patients requiring treatment interruptions due to adverse reactions in the combination arm was 79%. Treatment interruptions were part of the dose modification scheme for the combination therapy arm but not for the docetaxel monotherapy-treated patients.

Table 7 Percent Incidence of Adverse Events Considered Related or Unrelated to Treatment in ≥5% of Patients Participating in the XELODA and Docetaxel Combination vs Docetaxel Monotherapy Study
Adverse Event | XELODA 1250 mg/m^2/bid With Docetaxel 75 mg/m^2/3 weeks (n=251) |  |  | Docetaxel 100 mg/m^2/3 weeks (n=255)
 | Total % | Grade 3 % | Grade 4 % | Total % | Grade 3 % | Grade 4 %
Number of Patients With at Least One Adverse Event | 99 | 76.5 | 29.1 | 97 | 57.6 | 31.8
Body System/Adverse Event
GI
Diarrhea | 67 | 14 | <1 | 48 | 5 | <1
Stomatitis | 67 | 17 | <1 | 43 | 5 | –
Nausea | 45 | 7 | – | 36 | 2 | –
Vomiting | 35 | 4 | 1 | 24 | 2 | –
Constipation | 20 | 2 | – | 18 | – | –
Abdominal Pain | 30 | <3 | <1 | 24 | 2 | –
Dyspepsia | 14 | – | – | 8 | 1 | –
Dry Mouth | 6 | <1 | – | 5 | – | –
Skin and Subcutaneous
Hand-and-Foot Syndrome | 63 | 24 | NA | 8 | 1 | NA
Alopecia | 41 | 6 | – | 42 | 7 | –
Nail Disorder | 14 | 2 | – | 15 | – | –
Dermatitis | 8 | – | – | 11 | 1 | –
Rash Erythematous | 9 | <1 | – | 5 | – | –
Nail Discoloration | 6 | – | – | 4 | <1 | –
Onycholysis | 5 | 1 | – | 5 | 1 | –
Pruritus | 4 | – | – | 5 | – | –
General
Pyrexia | 28 | 2 | – | 34 | 2 | –
Asthenia | 26 | 4 | <1 | 25 | 6 | –
Fatigue | 22 | 4 | – | 27 | 6 | –
Weakness | 16 | 2 | – | 11 | 2 | –
Pain in Limb | 13 | <1 | – | 13 | 2 | –
Lethargy | 7 | – | – | 6 | 2 | –
Pain | 7 | <1 | – | 5 | 1 | –
Chest Pain (non-cardiac) | 4 | <1 | – | 6 | 2 | –
Influenza-like Illness | 5 | – | – | 5 | – | –
Neurological
Taste Disturbance | 16 | <1 | – | 14 | <1 | –
Headache | 15 | 3 | – | 15 | 2 | –
Paresthesia | 12 | <1 | – | 16 | 1 | –
Dizziness | 12 | – | – | 8 | <1 | –
Insomnia | 8 | – | – | 10 | <1 | –
Peripheral Neuropathy | 6 | – | – | 10 | 1 | –
Hypoaesthesia | 4 | <1 | – | 8 | <1 | –
Metabolism
Anorexia | 13 | 1 | – | 11 | <1 | –
Appetite Decreased | 10 | – | – | 5 | – | –
Weight Decreased | 7 | – | – | 5 | – | –
Dehydration | 10 | 2 | – | 7 | <1 | <1
Eye
Lacrimation Increased | 12 | – | – | 7 | <1 | –
Conjunctivitis | 5 | – | – | 4 | – | –
Eye Irritation | 5 | – | – | 1 | – | –
Musculoskeletal
Arthralgia | 15 | 2 | – | 24 | 3 | –
Myalgia | 15 | 2 | – | 25 | 2 | –
Back Pain | 12 | <1 | – | 11 | 3 | –
Bone Pain | 8 | <1 | – | 10 | 2 | –
Cardiac
Edema | 33 | <2 | – | 34 | <3 | 1
Blood
Neutropenic Fever | 16 | 3 | 13 | 21 | 5 | 16
Respiratory
Dyspnea | 14 | 2 | <1 | 16 | 2 | –
Cough | 13 | 1 | – | 22 | <1 | –
Sore Throat | 12 | 2 | – | 11 | <1 | –
Epistaxis | 7 | <1 | – | 6 | – | –
Rhinorrhea | 5 | – | – | 3 | – | –
Pleural Effusion | 2 | 1 | – | 7 | 4 | –
Infection
Oral Candidiasis | 7 | <1 | – | 8 | <1 | –
Urinary Tract Infection | 6 | <1 | – | 4 | – | –
Upper Respiratory Tract | 4 | – | – | 5 | 1 | –
Vascular
Flushing | 5 | – | – | 5 | – | –
Lymphoedema | 3 | <1 | – | 5 | 1 | –
Psychiatric
Depression | 5 | – | – | 5 | 1 | –
– Not observed
NA = Not Applicable

Table 8 Percent of Patients With Laboratory Abnormalities Participating in the XELODA and Docetaxel Combination vs Docetaxel Monotherapy Study
Adverse Event | XELODA 1250 mg/m^2/bid With Docetaxel 75 mg/m^2/3 weeks (n=251) |  |  | Docetaxel 100 mg/m^2/3 weeks (n=255)
Body System/Adverse Event | Total % | Grade 3 % | Grade 4 % | Total % | Grade 3 % | Grade 4 %
Hematologic
Leukopenia | 91 | 37 | 24 | 88 | 42 | 33
Neutropenia/Granulocytopenia | 86 | 20 | 49 | 87 | 10 | 66
Thrombocytopenia | 41 | 2 | 1 | 23 | 1 | 2
Anemia | 80 | 7 | 3 | 83 | 5 | <1
Lymphocytopenia | 99 | 48 | 41 | 98 | 44 | 40
Hepatobiliary
Hyperbilirubinemia | 20 | 7 | 2 | 6 | 2 | 2

Monotherapy

The following data are shown for the study in stage IV breast cancer patients who received a dose of 1250 mg/m^2 administered twice daily for 2 weeks followed by a 1-week rest period. The mean duration of treatment was 114 days. A total of 13 out of 162 patients (8%) discontinued treatment because of adverse reactions/intercurrent illness.

Table 9 Percent Incidence of Adverse Reactions Considered Remotely, Possibly or Probably Related to Treatment in ≥5% of Patients Participating in the Single Arm Trial in Stage IV Breast Cancer
Adverse Event | Phase 2 Trial in Stage IV Breast Cancer (n=162)
Body System/Adverse Event | Total % | Grade 3 % | Grade 4 %
GI
Diarrhea | 57 | 12 | 3
Nausea | 53 | 4 | –
Vomiting | 37 | 4 | –
Stomatitis | 24 | 7 | –
Abdominal Pain | 20 | 4 | –
Constipation | 15 | 1 | –
Dyspepsia | 8 | – | –
Skin and Subcutaneous
Hand-and-Foot Syndrome | 57 | 11 | NA
Dermatitis | 37 | 1 | –
Nail Disorder | 7 | – | –
General
Fatigue | 41 | 8 | –
Pyrexia | 12 | 1 | –
Pain in Limb | 6 | 1 | –
Neurological
Paresthesia | 21 | 1 | –
Headache | 9 | 1 | –
Dizziness | 8 | – | –
Insomnia | 8 | – | –
Metabolism
Anorexia | 23 | 3 | –
Dehydration | 7 | 4 | 1
Eye
Eye Irritation | 15 | – | –
Musculoskeletal
Myalgia | 9 | – | –
Cardiac
Edema | 9 | 1 | –
Blood
Neutropenia | 26 | 2 | 2
Thrombocytopenia | 24 | 3 | 1
Anemia | 72 | 3 | 1
Lymphopenia | 94 | 44 | 15
Hepatobiliary
Hyperbilirubinemia | 22 | 9 | 2
– Not observed
NA = Not Applicable

6.4 Clinically Relevant Adverse Events in <5% of Patients

Clinically relevant adverse events reported in <5% of patients treated with XELODA either as monotherapy or in combination with docetaxol that were considered at least remotely related to treatment are shown below; occurrences of each grade 3 and 4 adverse event are provided in parentheses.

Monotherapy (Metastatic Colorectal Cancer, Adjuvant Colorectal Cancer, Metastatic Breast Cancer)

Gastrointestinal: | abdominal distension, dysphagia, proctalgia, ascites (0.1%), gastric ulcer (0.1%), ileus (0.3%), toxic dilation of intestine, gastroenteritis (0.1%)
Skin & Subcutan.: | nail disorder (0.1%), sweating increased (0.1%), photosensitivity reaction (0.1%), skin ulceration, pruritus, radiation recall syndrome (0.2%)
General: | chest pain (0.2%), influenza-like illness, hot flushes, pain (0.1%), hoarseness, irritability, difficulty in walking, thirst, chest mass, collapse, fibrosis (0.1%), hemorrhage, edema, sedation
Neurological: | insomnia, ataxia (0.5%), tremor, dysphasia, encephalopathy (0.1%), abnormal coordination, dysarthria, loss of consciousness (0.2%), impaired balance
Metabolism: | increased weight, cachexia (0.4%), hypertriglyceridemia (0.1%), hypokalemia, hypomagnesemia
Eye: | conjunctivitis
Respiratory: | cough (0.1%), epistaxis (0.1%), asthma (0.2%), hemoptysis, respiratory distress (0.1%), dyspnea
Cardiac: | tachycardia (0.1%), bradycardia, atrial fibrillation, ventricular extrasystoles, extrasystoles, myocarditis (0.1%), pericardial effusion
Infections: | laryngitis (1.0%), bronchitis (0.2%), pneumonia (0.2%), bronchopneumonia (0.2%), keratoconjunctivitis, sepsis (0.3%), fungal infections (including candidiasis) (0.2%)
Musculoskeletal: | myalgia, bone pain (0.1%), arthritis (0.1%), muscle weakness
Blood & Lymphatic: | leukopenia (0.2%), coagulation disorder (0.1%), bone marrow depression (0.1%), idiopathic thrombocytopenia purpura (1.0%), pancytopenia (0.1%)
Vascular: | hypotension (0.2%), hypertension (0.1%), lymphoedema (0.1%), pulmonary embolism (0.2%), cerebrovascular accident (0.1%)
Psychiatric: | depression, confusion (0.1%)
Renal: | renal impairment (0.6%)
Ear: | vertigo
Hepatobiliary: | hepatic fibrosis (0.1%), hepatitis (0.1%), cholestatic hepatitis (0.1%), abnormal liver function tests
Immune System: | drug hypersensitivity (0.1%)
Postmarketing: | hepatic failure, lacrimal duct stenosis

XELODA In Combination With Docetaxel (Metastatic Breast Cancer)

Gastrointestinal: | ileus (0.4%), necrotizing enterocolitis (0.4%), esophageal ulcer (0.4%), hemorrhagic diarrhea (0.8%)
Neurological: | ataxia (0.4%), syncope (1.2%), taste loss (0.8%), polyneuropathy (0.4%), migraine (0.4%)
Cardiac: | supraventricular tachycardia (0.4%)
Infection: | neutropenic sepsis (2.4%), sepsis (0.4%), bronchopneumonia (0.4%)
Blood & Lymphatic: | agranulocytosis (0.4%), prothrombin decreased (0.4%)
Vascular: | hypotension (1.2%), venous phlebitis and thrombophlebitis (0.4%), postural hypotension (0.8%)
Renal: | renal failure (0.4%)
Hepatobiliary: | jaundice (0.4%), abnormal liver function tests (0.4%), hepatic failure (0.4%), hepatic coma (0.4%), hepatotoxicity (0.4%)
Immune System: | hypersensitivity (1.2%)

7 DRUG INTERACTIONS

7.1 Drug-Drug Interactions

Anticoagulants

Altered coagulation parameters and/or bleeding have been reported in patients taking XELODA concomitantly with coumarin-derivative anticoagulants such as warfarin and phenprocoumon [see Boxed Warning]. These events occurred within several days and up to several months after initiating XELODA therapy and, in a few cases, within 1 month after stopping XELODA. These events occurred in patients with and without liver metastases. In a drug interaction study with single-dose warfarin administration, there was a significant increase in the mean AUC of S-warfarin [see Clinical Pharmacology (12.3)]. The maximum observed INR value increased by 91%. This interaction is probably due to an inhibition of cytochrome P450 2C9 by capecitabine and/or its metabolites.

Phenytoin

The level of phenytoin should be carefully monitored in patients taking XELODA and phenytoin dose may need to be reduced [see Dosage and Administration (2.2)]. Postmarketing reports indicate that some patients receiving XELODA and phenytoin had toxicity associated with elevated phenytoin levels. Formal drug-drug interaction studies with phenytoin have not been conducted, but the mechanism of interaction is presumed to be inhibition of the CYP2C9 isoenzyme by capecitabine and/or its metabolites.

Leucovorin

The concentration of 5-fluorouracil is increased and its toxicity may be enhanced by leucovorin. Deaths from severe enterocolitis, diarrhea, and dehydration have been reported in elderly patients receiving weekly leucovorin and fluorouracil.

CYP2C9 substrates

Other than warfarin, no formal drug-drug interaction studies between XELODA and other CYP2C9 substrates have been conducted. Care should be exercised when XELODA is coadministered with CYP2C9 substrates.

7.2 Drug-Food Interaction

Food was shown to reduce both the rate and extent of absorption of capecitabine [see Clinical Pharmacology (12.3)]. In all clinical trials, patients were instructed to administer XELODA within 30 minutes after a meal. It is recommended that XELODA be administered with food [see Dosage and Administration (2)].

8 USE IN SPECIFIC POPULATIONS

8.1 Pregnancy: Category D

TERATOGENIC EFFECTS

XELODA can cause fetal harm when administered to a pregnant woman. Capecitabine at doses of 198 mg/kg/day during organogenesis caused malformations and embryo death in mice. In separate pharmacokinetic studies, this dose in mice produced 5'-DFUR AUC values about 0.2 times the corresponding values in patients administered the recommended daily dose. Malformations in mice included cleft palate, anophthalmia, microphthalmia, oligodactyly, polydactyly, syndactyly, kinky tail and dilation of cerebral ventricles. At doses of 90 mg/kg/day, capecitabine given to pregnant monkeys during organogenesis caused fetal death. This dose produced 5'-DFUR AUC values about 0.6 times the corresponding values in patients administered the recommended daily dose.

There are no adequate and well controlled studies of XELODA in pregnant women. If this drug is used during pregnancy, or if a patient becomes pregnant while receiving XELODA, the patient should be apprised of the potential hazard to the fetus. Women should be advised to avoid becoming pregnant while receiving treatment with XELODA [see Warnings and Precautions (5.6)].

8.3 Nursing Mothers

Lactating mice given a single oral dose of capecitabine excreted significant amounts of capecitabine metabolites into the milk. It is not known whether this drug is excreted in human milk. Because many drugs are excreted in human milk and because of the potential for serious adverse reactions in nursing infants from capecitabine, a decision should be made whether to discontinue nursing or to discontinue the drug, taking into account the importance of the drug to the mother.

8.4 Pediatric Use

The safety and effectiveness of XELODA in persons <18 years of age have not been established.

8.5 Geriatric Use

Physicians should pay particular attention to monitoring the adverse effects of XELODA in the elderly [see Warnings and Precautions (5.11)].

8.6 Hepatic Insufficiency

Exercise caution when patients with mild to moderate hepatic dysfunction due to liver metastases are treated with XELODA. The effect of severe hepatic dysfunction on XELODA is not known [see Warnings and Precautions (5.12) and Clinical Pharmacology (12.3)].

8.7 Renal Insufficiency

Patients with moderate (creatinine clearance = 30 to 50 mL/min) and severe (creatinine clearance <30 mL/min) renal impairment showed higher exposure for capecitabine, 5-FDUR, and FBAL than in those with normal renal function [see Contraindications (4.2), Warnings and Precautions (5.5), Dosage and Administration (2.3), and Clinical Pharmacology (12.3)].

10 OVERDOSAGE

The manifestations of acute overdose would include nausea, vomiting, diarrhea, gastrointestinal irritation and bleeding, and bone marrow depression. Medical management of overdose should include customary supportive medical interventions aimed at correcting the presenting clinical manifestations. Although no clinical experience using dialysis as a treatment for XELODA overdose has been reported, dialysis may be of benefit in reducing circulating concentrations of 5'-DFUR, a low–molecular-weight metabolite of the parent compound.

Single doses of XELODA were not lethal to mice, rats, and monkeys at doses up to 2000 mg/kg (2.4, 4.8, and 9.6 times the recommended human daily dose on a mg/m^2 basis).

11 DESCRIPTION

XELODA (capecitabine) is a fluoropyrimidine carbamate with antineoplastic activity. It is an orally administered systemic prodrug of 5'-deoxy-5-fluorouridine (5'-DFUR) which is converted to 5-fluorouracil.

The chemical name for capecitabine is 5'-deoxy-5-fluoro-N-[(pentyloxy) carbonyl]-cytidine and has a molecular weight of 359.35. Capecitabine has the following structural formula:

Capecitabine is a white to off-white crystalline powder with an aqueous solubility of 26 mg/mL at 20°C.

XELODA is supplied as biconvex, oblong film-coated tablets for oral administration. Each light peach-colored tablet contains 150 mg capecitabine and each peach-colored tablet contains 500 mg capecitabine. The inactive ingredients in XELODA include: anhydrous lactose, croscarmellose sodium, hydroxypropyl methylcellulose, microcrystalline cellulose, magnesium stearate and purified water. The peach or light peach film coating contains hydroxypropyl methylcellulose, talc, titanium dioxide, and synthetic yellow and red iron oxides.

12 CLINICAL PHARMACOLOGY

12.1 Mechanism of Action

Enzymes convert capecitabine to 5-fluorouracil (5-FU) in vivo. Both normal and tumor cells metabolize 5-FU to 5-fluoro-2'-deoxyuridine monophosphate (FdUMP) and 5-fluorouridine triphosphate (FUTP). These metabolites cause cell injury by two different mechanisms. First, FdUMP and the folate cofactor, N^5-10-methylenetetrahydrofolate, bind to thymidylate synthase (TS) to form a covalently bound ternary complex. This binding inhibits the formation of thymidylate from 2'-deoxyuridylate. Thymidylate is the necessary precursor of thymidine triphosphate, which is essential for the synthesis of DNA, so that a deficiency of this compound can inhibit cell division. Second, nuclear transcriptional enzymes can mistakenly incorporate FUTP in place of uridine triphosphate (UTP) during the synthesis of RNA. This metabolic error can interfere with RNA processing and protein synthesis.

12.3 Pharmacokinetics

Absorption

Following oral administration of 1255 mg/m^2 BID to cancer patients, capecitabine reached peak blood levels in about 1.5 hours (Tmax) with peak 5-FU levels occurring slightly later, at 2 hours. Food reduced both the rate and extent of absorption of capecitabine with mean Cmax and AUC0-∞ decreased by 60% and 35%, respectively. The Cmax and AUC0-∞ of 5-FU were also reduced by food by 43% and 21%, respectively. Food delayed Tmax of both parent and 5-FU by 1.5 hours [see Warnings and Precautions (5), Dosage and Administration (2), and Drug-Food Interaction (7.2)].

The pharmacokinetics of XELODA and its metabolites have been evaluated in about 200 cancer patients over a dosage range of 500 to 3500 mg/m^2/day. Over this range, the pharmacokinetics of XELODA and its metabolite, 5'-DFCR were dose proportional and did not change over time. The increases in the AUCs of 5'-DFUR and 5-FU, however, were greater than proportional to the increase in dose and the AUC of 5-FU was 34% higher on day 14 than on day 1. The interpatient variability in the Cmax and AUC of 5-FU was greater than 85%.

Distribution

Plasma protein binding of capecitabine and its metabolites is less than 60% and is not concentration-dependent. Capecitabine was primarily bound to human albumin (approximately 35%). XELODA has a low potential for pharmacokinetic interactions related to plasma protein binding.

Bioactivation and Metabolism

Capecitabine is extensively metabolized enzymatically to 5-FU. In the liver, a 60 kDa carboxylesterase hydrolyzes much of the compound to 5'-deoxy-5-fluorocytidine (5'-DFCR). Cytidine deaminase, an enzyme found in most tissues, including tumors, subsequently converts 5'-DFCR to 5'-DFUR. The enzyme, thymidine phosphorylase (dThdPase), then hydrolyzes 5'-DFUR to the active drug 5-FU. Many tissues throughout the body express thymidine phosphorylase. Some human carcinomas express this enzyme in higher concentrations than surrounding normal tissues. Following oral administration of XELODA 7 days before surgery in patients with colorectal cancer, the median ratio of 5-FU concentration in colorectal tumors to adjacent tissues was 2.9 (range from 0.9 to 8.0). These ratios have not been evaluated in breast cancer patients or compared to 5-FU infusion.

Metabolic Pathway of capecitabine to 5-FU

The enzyme dihydropyrimidine dehydrogenase hydrogenates 5-FU, the product of capecitabine metabolism, to the much less toxic 5-fluoro-5, 6-dihydro-fluorouracil (FUH2). Dihydropyrimidinase cleaves the pyrimidine ring to yield 5-fluoro-ureido-propionic acid (FUPA). Finally, β-ureido-propionase cleaves FUPA to α-fluoro-β-alanine (FBAL) which is cleared in the urine.

In vitro enzymatic studies with human liver microsomes indicated that capecitabine and its metabolites (5'-DFUR, 5'-DFCR, 5-FU, and FBAL) did not inhibit the metabolism of test substrates by cytochrome P450 isoenzymes 1A2, 2A6, 3A4, 2C19, 2D6, and 2E1.

Excretion

Capecitabine and its metabolites are predominantly excreted in urine; 95.5% of administered capecitabine dose is recovered in urine. Fecal excretion is minimal (2.6%). The major metabolite excreted in urine is FBAL which represents 57% of the administered dose. About 3% of the administered dose is excreted in urine as unchanged drug. The elimination half-life of both parent capecitabine and 5-FU was about 0.75 hour.

Effect of Age, Gender, and Race on the Pharmacokinetics of Capecitabine

A population analysis of pooled data from the two large controlled studies in patients with metastatic colorectal cancer (n=505) who were administered XELODA at 1250 mg/m^2 twice a day indicated that gender (202 females and 303 males) and race (455 white/Caucasian patients, 22 black patients, and 28 patients of other race) have no influence on the pharmacokinetics of 5'-DFUR, 5-FU and FBAL. Age has no significant influence on the pharmacokinetics of 5'-DFUR and 5-FU over the range of 27 to 86 years. A 20% increase in age results in a 15% increase in AUC of FBAL [see Warnings and Precautions (5.11) and Dosage and Administration (2.3)].

Following oral administration of 825 mg/m^2 capecitabine twice daily for 14 days, Japanese patients (n=18) had about 36% lower Cmax and 24% lower AUC for capecitabine than the Caucasian patients (n=22). Japanese patients had also about 25% lower Cmax and 34% lower AUC for FBAL than the Caucasian patients. The clinical significance of these differences is unknown. No significant differences occurred in the exposure to other metabolites (5'-DFCR, 5'-DFUR, and 5-FU).

Effect of Hepatic Insufficiency

XELODA has been evaluated in 13 patients with mild to moderate hepatic dysfunction due to liver metastases defined by a composite score including bilirubin, AST/ALT and alkaline phosphatase following a single 1255 mg/m^2 dose of XELODA. Both AUC0-∞ and Cmax of capecitabine increased by 60% in patients with hepatic dysfunction compared to patients with normal hepatic function (n=14). The AUC0-∞ and Cmax of 5-FU were not affected. In patients with mild to moderate hepatic dysfunction due to liver metastases, caution should be exercised when XELODA is administered. The effect of severe hepatic dysfunction on XELODA is not known [see Warnings and Precautions (5.11) and Use in Special Populations (8.6)].

Effect of Renal Insufficiency

Following oral administration of 1250 mg/m^2 capecitabine twice a day to cancer patients with varying degrees of renal impairment, patients with moderate (creatinine clearance = 30 to 50 mL/min) and severe (creatinine clearance <30 mL/min) renal impairment showed 85% and 258% higher systemic exposure to FBAL on day 1 compared to normal renal function patients (creatinine clearance >80 mL/min). Systemic exposure to 5'-DFUR was 42% and 71% greater in moderately and severely renal impaired patients, respectively, than in normal patients. Systemic exposure to capecitabine was about 25% greater in both moderately and severely renal impaired patients [see Dosage and Administration (2.3), Contraindications (4.2), Warnings and Precautions (5.5), and Use in Special Populations (8.7)].

Effect of Capecitabine on the Pharmacokinetics of Warfarin

In four patients with cancer, chronic administration of capecitabine (1250 mg/m^2 bid) with a single 20 mg dose of warfarin increased the mean AUC of S-warfarin by 57% and decreased its clearance by 37%. Baseline corrected AUC of INR in these 4 patients increased by 2.8-fold, and the maximum observed mean INR value was increased by 91% [see Boxed Warning and Drug Interactions (7.1)].

Effect of Antacids on the Pharmacokinetics of Capecitabine

When Maalox® (20 mL), an aluminum hydroxide- and magnesium hydroxide-containing antacid, was administered immediately after XELODA (1250 mg/m^2, n=12 cancer patients), AUC and Cmax increased by 16% and 35%, respectively, for capecitabine and by 18% and 22%, respectively, for 5'-DFCR. No effect was observed on the other three major metabolites (5'-DFUR, 5-FU, FBAL) of XELODA.

Effect of Capecitabine on the Pharmacokinetics of Docetaxel and Vice Versa

A Phase 1 study evaluated the effect of XELODA on the pharmacokinetics of docetaxel (Taxotere®) and the effect of docetaxel on the pharmacokinetics of XELODA was conducted in 26 patients with solid tumors. XELODA was found to have no effect on the pharmacokinetics of docetaxel (Cmax and AUC) and docetaxel has no effect on the pharmacokinetics of capecitabine and the 5-FU precursor 5'-DFUR.

13 NONCLINICAL TOXICOLOGY

13.1 Carcinogenesis, Mutagenesis, Impairment of Fertility

Adequate studies investigating the carcinogenic potential of XELODA have not been conducted. Capecitabine was not mutagenic in vitro to bacteria (Ames test) or mammalian cells (Chinese hamster V79/HPRT gene mutation assay). Capecitabine was clastogenic in vitro to human peripheral blood lymphocytes but not clastogenic in vivo to mouse bone marrow (micronucleus test). Fluorouracil causes mutations in bacteria and yeast. Fluorouracil also causes chromosomal abnormalities in the mouse micronucleus test in vivo.

Impairment of Fertility

In studies of fertility and general reproductive performance in female mice, oral capecitabine doses of 760 mg/kg/day (about 2300 mg/m^2/day) disturbed estrus and consequently caused a decrease in fertility. In mice that became pregnant, no fetuses survived this dose. The disturbance in estrus was reversible. In males, this dose caused degenerative changes in the testes, including decreases in the number of spermatocytes and spermatids. In separate pharmacokinetic studies, this dose in mice produced 5'-DFUR AUC values about 0.7 times the corresponding values in patients administered the recommended daily dose.

14 CLINICAL STUDIES

14.1 Adjuvant Colon Cancer

A multicenter randomized, controlled phase 3 clinical trial in patients with Dukes' C colon cancer (X-ACT) provided data concerning the use of XELODA for the adjuvant treatment of patients with colon cancer. The primary objective of the study was to compare disease-free survival (DFS) in patients receiving XELODA to those receiving IV 5-FU/LV alone. In this trial, 1987 patients were randomized either to treatment with XELODA 1250 mg/m^2 orally twice daily for 2 weeks followed by a 1-week rest period, given as 3-week cycles for a total of 8 cycles (24 weeks) or IV bolus 5-FU 425 mg/m^2 and 20 mg/m^2 IV leucovorin on days 1 to 5, given as 4-week cycles for a total of 6 cycles (24 weeks). Patients in the study were required to be between 18 and 75 years of age with histologically-confirmed Dukes' stage C colon cancer with at least one positive lymph node and to have undergone (within 8 weeks prior to randomization) complete resection of the primary tumor without macroscopic or microscopic evidence of remaining tumor. Patients were also required to have no prior cytotoxic chemotherapy or immunotherapy (except steroids), and have an ECOG performance status of 0 or 1 (KPS ≥ 70%), ANC ≥ 1.5×10^9/L, platelets ≥ 100×10^9/L, serum creatinine ≤ 1.5 ULN, total bilirubin ≤ 1.5 ULN, AST/ALT ≤ 2.5 ULN and CEA within normal limits at time of randomization.

The baseline demographics for XELODA and 5-FU/LV patients are shown in Table 10. The baseline characteristics were well-balanced between arms.

Table 10 Baseline Demographics
 | XELODA (n=1004) | 5-FU/LV (n=983)
Age (median, years) | 62 | 63
Range | (25-80) | (22-82)
Gender
Male (n, %) | 542 (54) | 532 (54)
Female (n, %) | 461 (46) | 451 (46)
ECOG PS
0 (n, %) | 849 (85) | 830 (85)
1 (n, %) | 152 (15) | 147 (15)
Staging – Primary Tumor
PT1 (n, %) | 12 (1) | 6 (0.6)
PT2 (n, %) | 90 (9) | 92 (9)
PT3 (n, %) | 763 (76) | 746 (76)
PT4 (n, %) | 138 (14) | 139 (14)
Other (n, %) | 1 (0.1) | 0 (0)
Staging – Lymph Node
pN1 (n, %) | 695 (69) | 694 (71)
pN2 (n, %) | 305 (30) | 288 (29)
Other (n, %) | 4 (0.4) | 1 (0.1)

All patients with normal renal function or mild renal impairment began treatment at the full starting dose of 1250 mg/m^2 orally twice daily. The starting dose was reduced in patients with moderate renal impairment (calculated creatinine clearance 30 to 50 mL/min) at baseline [see Dosage and Administration (2.3)]. Subsequently, for all patients, doses were adjusted when needed according to toxicity. Dose management for XELODA included dose reductions, cycle delays and treatment interruptions (see Table 11).

Table 11 Summary of Dose Modifications in X-ACT Study
 | XELODA N = 995 | 5-FU/LV N = 974
Median relative dose intensity (%) | 93 | 92
Patients completing full course of treatment (%) | 83 | 87
Patients with treatment interruption (%) | 15 | 5
Patients with cycle delay (%) | 46 | 29
Patients with dose reduction (%) | 42 | 44
Patients with treatment interruption, cycle delay, or dose reduction (%) | 57 | 52

The median follow-up at the time of the analysis was 83 months (6.9 years). The hazard ratio for DFS for XELODA compared to 5-FU/LV was 0.88 (95% C.I. 0.77 – 1.01) (see Table 12 and Figure 1). Because the upper 2-sided 95% confidence limit of hazard ratio was less than 1.20, XELODA was non-inferior to 5-FU/LV. The choice of the non-inferiority margin of 1.20 corresponds to the retention of approximately 75% of the 5-FU/LV effect on DFS. The hazard ratio for XELODA compared to 5-FU/LV with respect to overall survival was 0.86 (95% C.I. 0.74 – 1.01). The 5-year overall survival rates were 71.4% for XELODA and 68.4% for 5-FU/LV (see Figure 2).

Table 12 Efficacy of XELODA vs 5-FU/LV in Adjuvant Treatment of Colon Cancer
All Randomized Population | XELODA (n=1004) | 5-FU/LV (n=983)
Median follow-up (months) | 83 | 83
5-year Disease-free Survival Rates (%) | 59.1 | 54.6
Hazard Ratio | 0.88
(XELODA/5-FU/LV) | (0.77 - 1.01)
(95% C.I. for Hazard Ratio)
p-value | p = 0.068

Figure 1 Kaplan-Meier Estimates of Disease-Free Survival (All Randomized Population) [XELODA has been demonstrated to be non-inferior to 5-FU/LV.]

Figure 2 Kaplan-Meier Estimates of Overall Survival (All Randomized Population)

14.2 Metastatic Colorectal Cancer

General

The recommended dose of XELODA was determined in an open-label, randomized clinical study, exploring the efficacy and safety of continuous therapy with capecitabine (1331 mg/m^2/day in two divided doses, n=39), intermittent therapy with capecitabine (2510 mg/m^2/day in two divided doses, n=34), and intermittent therapy with capecitabine in combination with oral leucovorin (LV) (capecitabine 1657 mg/m^2/day in two divided doses, n=35; leucovorin 60 mg/day) in patients with advanced and/or metastatic colorectal carcinoma in the first-line metastatic setting. There was no apparent advantage in response rate to adding leucovorin to XELODA; however, toxicity was increased. XELODA, 1250 mg/m^2 twice daily for 14 days followed by a 1-week rest, was selected for further clinical development based on the overall safety and efficacy profile of the three schedules studied.

Monotherapy

Data from two open-label, multicenter, randomized, controlled clinical trials involving 1207 patients support the use of XELODA in the first-line treatment of patients with metastatic colorectal carcinoma. The two clinical studies were identical in design and were conducted in 120 centers in different countries. Study 1 was conducted in the US, Canada, Mexico, and Brazil; Study 2 was conducted in Europe, Israel, Australia, New Zealand, and Taiwan. Altogether, in both trials, 603 patients were randomized to treatment with XELODA at a dose of 1250 mg/m^2 twice daily for 2 weeks followed by a 1-week rest period and given as 3-week cycles; 604 patients were randomized to treatment with 5-FU and leucovorin (20 mg/m^2 leucovorin IV followed by 425 mg/m^2 IV bolus 5-FU, on days 1 to 5, every 28 days).

In both trials, overall survival, time to progression and response rate (complete plus partial responses) were assessed. Responses were defined by the World Health Organization criteria and submitted to a blinded independent review committee (IRC). Differences in assessments between the investigator and IRC were reconciled by the sponsor, blinded to treatment arm, according to a specified algorithm. Survival was assessed based on a non-inferiority analysis.

The baseline demographics for XELODA and 5-FU/LV patients are shown in Table 13.

Table 13 Baseline Demographics of Controlled Colorectal Trials
 | Study 1 |  | Study 2
 | XELODA (n=302) | 5-FU/LV (n=303) | XELODA (n=301) | 5-FU/LV (n=301)
Age (median, years) | 64 | 63 | 64 | 64
Range | (23-86) | (24-87) | (29-84) | (36-86)
Gender
Male (%) | 181 (60) | 197 (65) | 172 (57) | 173 (57)
Female (%) | 121 (40) | 106 (35) | 129 (43) | 128 (43)
Karnofsky PS (median) | 90 | 90 | 90 | 90
Range | (70-100) | (70-100) | (70-100) | (70-100)
Colon (%) | 222 (74) | 232 (77) | 199 (66) | 196 (65)
Rectum (%) | 79 (26) | 70 (23) | 101 (34) | 105 (35)
Prior radiation therapy (%) | 52 (17) | 62 (21) | 42 (14) | 42 (14)
Prior adjuvant 5-FU (%) | 84 (28) | 110 (36) | 56 (19) | 41 (14)

The efficacy endpoints for the two phase 3 trials are shown in Table 14 and Table 15.

Table 14 Efficacy of XELODA vs 5-FU/LV in Colorectal Cancer (Study 1)
 | XELODA (n=302) | 5-FU/LV (n=303)
Overall Response Rate (%, 95% C.I.) | 21 (16-26) | 11 (8-15)
(p-value) | 0.0014
Time to Progression (Median, days, 95% C.I.) | 128 (120-136) | 131 (105-153)
Hazard Ratio (XELODA/5-FU/LV) | 0.99
95% C.I. for Hazard Ratio | (0.84-1.17)
Survival (Median, days, 95% C.I.) | 380 (321-434) | 407 (366-446)
Hazard Ratio (XELODA/5-FU/LV) | 1.00
95% C.I. for Hazard Ratio | (0.84-1.18)

Table 15 Efficacy of XELODA vs 5-FU/LV in Colorectal Cancer (Study 2)
 | XELODA (n=301) | 5-FU/LV (n=301)
Overall Response Rate (%, 95% C.I.) | 21 (16-26) | 14 (10-18)
(p-value) | 0.027
Time to Progression (Median, days, 95% C.I.) | 137 (128-165) | 131 (102-156)
Hazard Ratio (XELODA/5-FU/LV) | 0.97
95% C.I. for Hazard Ratio | (0.82-1.14)
Survival (Median, days, 95% C.I.) | 404 (367-452) | 369 (338-430)
Hazard Ratio (XELODA/5-FU/LV) | 0.92
95% C.I. for Hazard Ratio | (0.78-1.09)

Figure 3 Kaplan-Meier Curve for Overall Survival of Pooled Data (Studies 1 and 2)

XELODA was superior to 5-FU/LV for objective response rate in Study 1 and Study 2. The similarity of XELODA and 5-FU/LV in these studies was assessed by examining the potential difference between the two treatments. In order to assure that XELODA has a clinically meaningful survival effect, statistical analyses were performed to determine the percent of the survival effect of 5-FU/LV that was retained by XELODA. The estimate of the survival effect of 5-FU/LV was derived from a meta-analysis of ten randomized studies from the published literature comparing 5-FU to regimens of 5-FU/LV that were similar to the control arms used in these Studies 1 and 2. The method for comparing the treatments was to examine the worst case (95% confidence upper bound) for the difference between 5-FU/LV and XELODA, and to show that loss of more than 50% of the 5-FU/LV survival effect was ruled out. It was demonstrated that the percent of the survival effect of 5-FU/LV maintained was at least 61% for Study 2 and 10% for Study 1. The pooled result is consistent with a retention of at least 50% of the effect of 5-FU/LV. It should be noted that these values for preserved effect are based on the upper bound of the 5-FU/LV vs XELODA difference. These results do not exclude the possibility of true equivalence of XELODA to 5-FU/LV (see Table 14, Table 15, and Figure 3).

14.3 Breast Cancer

XELODA has been evaluated in clinical trials in combination with docetaxel (Taxotere®) and as monotherapy.

In Combination With Docetaxel

The dose of XELODA used in the phase 3 clinical trial in combination with docetaxel was based on the results of a phase 1 study, where a range of doses of docetaxel administered in 3-week cycles in combination with an intermittent regimen of XELODA (14 days of treatment, followed by a 7-day rest period) were evaluated. The combination dose regimen was selected based on the tolerability profile of the 75 mg/m^2 administered in 3-week cycles of docetaxel in combination with 1250 mg/m^2 twice daily for 14 days of XELODA administered in 3-week cycles. The approved dose of 100 mg/m^2 of docetaxel administered in 3-week cycles was the control arm of the phase 3 study.

XELODA in combination with docetaxel was assessed in an open-label, multicenter, randomized trial in 75 centers in Europe, North America, South America, Asia, and Australia. A total of 511 patients with metastatic breast cancer resistant to, or recurring during or after an anthracycline-containing therapy, or relapsing during or recurring within 2 years of completing an anthracycline-containing adjuvant therapy were enrolled. Two hundred and fifty-five (255) patients were randomized to receive XELODA 1250 mg/m^2 twice daily for 14 days followed by 1 week without treatment and docetaxel 75 mg/m^2 as a 1-hour intravenous infusion administered in 3-week cycles. In the monotherapy arm, 256 patients received docetaxel 100 mg/m^2 as a 1-hour intravenous infusion administered in 3-week cycles. Patient demographics are provided in Table 16.

Table 16 Baseline Demographics and Clinical Characteristics XELODA and Docetaxel Combination vs Docetaxel in Breast Cancer Trial
 | XELODA + Docetaxel (n=255) | Docetaxel (n=256)
Age (median, years) | 52 | 51
Karnofsky PS (median) | 90 | 90
Site of Disease
Lymph nodes | 121 (47%) | 125 (49%)
Liver | 116 (45%) | 122 (48%)
Bone | 107 (42%) | 119 (46%)
Lung | 95 (37%) | 99 (39%)
Skin | 73 (29%) | 73 (29%)
Prior Chemotherapy
Anthracycline | 255 (100%) | 256 (100%)
5-FU | 196 (77%) | 189 (74%)
Paclitaxel | 25 (10%) | 22 (9%)
Resistance to an Anthracycline
No resistance | 19 (7%) | 19 (7%)
Progression on anthracycline therapy | 65 (26%) | 73 (29%)
Stable disease after 4 cycles of anthracycline therapy | 41 (16%) | 40 (16%)
Relapsed within 2 years of completion of anthracycline-adjuvant therapy | 78 (31%) | 74 (29%)
Experienced a brief response to anthracycline therapy, with subsequent progression while on therapy or within 12 months after last dose | 51 (20%) | 50 (20%)
No. of Prior Chemotherapy Regimens for Treatment of Metastatic Disease
0 | 89 (35%) | 80 (31%)
1 | 123 (48%) | 135 (53%)
2 | 43 (17%) | 39 (15%)
3 | 0 (0%) | 2 (1%)

XELODA in combination with docetaxel resulted in statistically significant improvement in time to disease progression, overall survival and objective response rate compared to monotherapy with docetaxel as shown in Table 17, Figure 4, and Figure 5.

Table 17 Efficacy of XELODA and Docetaxel Combination vs Docetaxel Monotherapy
Efficacy Parameter | Combination Therapy | Monotherapy | p-value | Hazard Ratio
Time to Disease Progression
Median Days | 186 | 128 | 0.0001 | 0.643
95% C.I. | (165-198) | (105-136)
Overall Survival
Median Days | 442 | 352 | 0.0126 | 0.775
95% C.I. | (375-497) | (298-387)
Response Rate | 32% | 22% | 0.009 | NA

Figure 4 Kaplan-Meier Estimates for Time to Disease Progression XELODA and Docetaxel vs Docetaxel

Figure 5 Kaplan-Meier Estimates of Survival XELODA and Docetaxel vs Docetaxel

Monotherapy

The antitumor activity of XELODA as a monotherapy was evaluated in an open-label single-arm trial conducted in 24 centers in the US and Canada. A total of 162 patients with stage IV breast cancer were enrolled. The primary endpoint was tumor response rate in patients with measurable disease, with response defined as a ≥50% decrease in sum of the products of the perpendicular diameters of bidimensionally measurable disease for at least 1 month. XELODA was administered at a dose of 1255 mg/m^2 twice daily for 2 weeks followed by a 1-week rest period and given as 3-week cycles. The baseline demographics and clinical characteristics for all patients (n=162) and those with measurable disease (n=135) are shown in Table 18. Resistance was defined as progressive disease while on treatment, with or without an initial response, or relapse within 6 months of completing treatment with an anthracycline-containing adjuvant chemotherapy regimen.

Table 18 Baseline Demographics and Clinical Characteristics Single-Arm Breast Cancer Trial
 | Patients With Measurable Disease (n=135) | All Patients (n=162)
Age (median, years) | 55 | 56
Karnofsky PS | 90 | 90
No. Disease Sites
1-2 | 43 (32%) | 60 (37%)
3-4 | 63 (46%) | 69 (43%)
>5 | 29 (22%) | 34 (21%)
Dominant Site of Disease
Visceral | 101 (75%) | 110 (68%)
Soft Tissue | 30 (22%) | 35 (22%)
Bone | 4 (3%) | 17 (10%)
Prior Chemotherapy
Paclitaxel | 135 (100%) | 162 (100%)
Anthracycline [Includes 2 patients treated with an anthracenedione] | 122 (90%) | 147 (91%)
5-FU | 110 (81%) | 133 (82%)
Resistance to Paclitaxel | 103 (76%) | 124 (77%)
Resistance to an Anthracycline | 55 (41%) | 67 (41%)
Resistance to both Paclitaxel and an Anthracycline | 43 (32%) | 51 (31%)

Antitumor responses for patients with disease resistant to both paclitaxel and an anthracycline are shown in Table 19.

Table 19 Response Rates in Doubly-Resistant Patients Single-Arm Breast Cancer Trial
 | Resistance to Both Paclitaxel and an Anthracycline (n=43)
CR | 0
PR [Includes 2 patients treated with an anthracenedione] | 11
CR + PR | 11
Response Rate | 25.6%
(95% C.I.) | (13.5, 41.2)
Duration of Response,
Median in days | 154
(Range) | (63-233)

For the subgroup of 43 patients who were doubly resistant, the median time to progression was 102 days and the median survival was 255 days. The objective response rate in this population was supported by a response rate of 18.5% (1 CR, 24 PRs) in the overall population of 135 patients with measurable disease, who were less resistant to chemotherapy (see Table 18). The median time to progression was 90 days and the median survival was 306 days.

15 REFERENCES

1. NIOSH Alert: Preventing occupational exposures to antineoplastic and other hazardous drugs in healthcare settings. 2004. U.S. Department of Health and Human Services, Public Health Service, Centers for Disease Control and Prevention, National Institute for Occupational Safety and Health, DHHS (NIOSH) Publication No. 2004-165.
2. OSHA Technical Manual, TED 1-0.15A, Section VI: Chapter 2. Controlling Occupational Exposure to Hazardous Drugs. OSHA, 1999. http://www.osha.gov/dts/osta/otm/otm_vi/otm_vi_2.html
3. American Society of Health-System Pharmacists. ASHP Guidelines on Handling Hazardous Drugs: Am J Health-Syst Pharm. 2006;63:1172-1193.
4. Polovich M., White JM, Kelleher LO (eds). Chemotherapy and biotherapy guidelines and recommendations for practice (2nd ed.) 2005. Pittsburgh, PA: Oncology Nursing Society.

16 HOW SUPPLIED/STORAGE AND HANDLING

150 mg

Color: Light peach

Engraving: XELODA on one side and 150 on the other 150 mg tablets are packaged in

Bottles of 60 | NDC 54868-4143-0

500 mg

Color: Peach

Engraving: XELODA on one side and 500 on the other 500 mg tablets are packaged in

Bottles of 20 | NDC 54868-5260-9
Bottles of 28 | NDC 54868-5260-5
Bottles of 30 | NDC 54868-5260-0
Bottles of 60 | NDC 54868-5260-1
Bottles of 90 | NDC 54868-5260-3
Bottles of 120 | NDC 54868-5260-2

Storage and Handling

Store at 25°C (77°F); excursions permitted to 15° to 30°C (59° to 86°F). [See USP Controlled Room Temperature]. KEEP TIGHTLY CLOSED.

Care should be exercised in the handling of XELODA. XELODA tablets should not be cut or crushed. The use of gloves and safety glasses is recommended to avoid exposure in case of breakage of tablets. If powder from broken XELODA tablets contacts the skin, wash the skin immediately and thoroughly with soap and water. If XELODA contacts the mucous membranes, flush thoroughly with water.

Procedures for the proper handling and disposal of anticancer drugs should be considered. Several guidelines on the subject have been published.^1-4

17 PATIENT COUNSELING INFORMATION

17.1 Information for Patients

(see Patient Package Insert)

Patients and patients' caregivers should be informed of the expected adverse effects of XELODA, particularly nausea, vomiting, diarrhea, and hand-and-foot syndrome, and should be made aware that patient-specific dose adaptations during therapy are expected and necessary [see Dosage and Administration (2.2)]. As described below, patients taking XELODA should be informed of the need to interrupt treatment immediately if moderate or severe toxicity occurs. Patients should be encouraged to recognize the common grade 2 toxicities associated with XELODA treatment.

Diarrhea

Patients experiencing grade 2 diarrhea (an increase of 4 to 6 stools/day or nocturnal stools) or greater should be instructed to stop taking XELODA immediately. Standard antidiarrheal treatments (eg, loperamide) are recommended.

Nausea

Patients experiencing grade 2 nausea (food intake significantly decreased but able to eat intermittently) or greater should be instructed to stop taking XELODA immediately. Initiation of symptomatic treatment is recommended.

Vomiting

Patients experiencing grade 2 vomiting (2 to 5 episodes in a 24-hour period) or greater should be instructed to stop taking XELODA immediately. Initiation of symptomatic treatment is recommended.

Hand-and-Foot Syndrome

Patients experiencing grade 2 hand-and-foot syndrome (painful erythema and swelling of the hands and/or feet and/or discomfort affecting the patients' activities of daily living) or greater should be instructed to stop taking XELODA immediately.

Stomatitis

Patients experiencing grade 2 stomatitis (painful erythema, edema or ulcers of the mouth or tongue, but able to eat) or greater should be instructed to stop taking XELODA immediately. Initiation of symptomatic treatment is recommended [see Dosage and Administration (2.2)].

Fever and Neutropenia

Patients who develop a fever of 100.5°F or greater or other evidence of potential infection should be instructed to call their physician.

PATIENT INFORMATION

Read this leaflet before you start taking XELODA® [zeh-LOE-duh] and each time you refill your prescription in case the information has changed. This leaflet contains important information about XELODA. However, this information does not take the place of talking with your doctor. This information cannot cover all possible risks and benefits of XELODA. Your doctor should always be your first choice for discussing your medical condition and this medicine.

What is XELODA?

XELODA is a medicine you take by mouth (orally). XELODA is changed in the body to 5-fluorouracil (5-FU). In some patients with colon, rectum or breast cancer, 5-FU stops cancer cells from growing and decreases the size of the tumor.

XELODA is used to treat:

- cancer of the colon after surgery
- cancer of the colon or rectum (colorectal cancer) that has spread to other parts of the body (metastatic colorectal cancer). You should know that in studies, other medicines showed improved survival when they were taken together with 5-FU and leucovorin. In studies, XELODA was no worse than 5-FU and leucovorin taken together but did not improve survival compared to these two medicines.
- breast cancer that has spread to other parts of the body (metastatic breast cancer) together with another medicine called docetaxel (TAXOTERE ®)
- breast cancer that has spread to other parts of the body and has not improved after treatment with other medicines such as paclitaxel (TAXOL ®) and anthracycline-containing medicine such as Adriamycin™ and doxorubicin

What is the most important information about XELODA?

XELODA may increase the effect of other medicines used to thin your blood such as warfarin (COUMADIN®). It is very important that your doctor knows if you are taking a blood thinner such as warfarin because XELODA may increase the effect of this medicine and could lead to serious side effects. If you are taking blood thinners and XELODA, your doctor needs to check more often how fast your blood clots and change the dose of the blood thinner, if needed.

Who should not take XELODA?

1. DO NOT TAKE XELODA IF YOU
  - are nursing a baby. Tell your doctor if you are nursing. XELODA may pass to the baby in your milk and harm the baby.
  - are allergic to 5-fluorouracil
  - are allergic to capecitabine or to any of the ingredients in XELODA
  - have been told that you lack the enzyme DPD (dihydropyrimidine dehydrogenase)
2. TELL YOUR DOCTOR IF YOU
  - take a blood thinner such as warfarin (COUMADIN). This is very important because XELODA may increase the effect of the blood thinner. If you are taking blood thinners and XELODA, your doctor needs to check more often how fast your blood clots and change the dose of the blood thinner, if needed.
  - take phenytoin (DILANTIN®). Your doctor needs to test the levels of phenytoin in your blood more often or change your dose of phenytoin.
  - are pregnant or think you may be pregnant. XELODA may harm your unborn child.
  - have kidney problems. Your doctor may prescribe a different medicine or lower the XELODA dose.
  - have liver problems. You may need to be checked for liver problems while you take XELODA.
  - have heart problems because you could have more side effects related to your heart.
  - take the vitamin folic acid. It may affect how XELODA works.

How should I take XELODA?

Take XELODA exactly as your doctor tells you to. Your doctor will prescribe a dose and treatment plan that is right for you. Your doctor may want you to take both 150 mg and 500 mg tablets together for each dose. If so, you must be able to identify the tablets. Taking the wrong tablets could cause an overdose (too much medicine) or underdose (too little medicine). The 150 mg tablets are light peach in color with 150 on one side. The 500 mg tablets are peach in color with 500 on one side. Your doctor may change the amount of medicine you take during your treatment. Your doctor may prescribe XELODA Tablets with docetaxel (TAXOTERE) injection.

- XELODA is taken in 2 daily doses, a morning dose and an evening dose
- Take XELODA tablets within 30 minutes after the end of a meal (breakfast and dinner)
- Swallow XELODA tablets whole with water
- If you miss a dose of XELODA, do not take the missed dose at all and do not double the next dose. Instead, continue your regular dosing schedule and check with your doctor.
- XELODA is usually taken for 14 days followed by a 7-day rest period (no drug), for a 21-day cycle. Your doctor will tell you how many cycles of treatment you will need.
- If you take too much XELODA, contact your doctor or local poison control center or emergency room right away.

What should I avoid while taking XELODA?

- Women should not become pregnant while taking XELODA. XELODA may harm your unborn child. Use effective birth control while taking XELODA. Tell your doctor if you become pregnant.
- Do not breast-feed. XELODA may pass through your milk and harm your baby.
- Men should use birth control while taking XELODA

What are the most common side effects of XELODA?

The most common side effects of XELODA are:

- diarrhea, nausea, vomiting, sores in the mouth and throat (stomatitis), stomach area pain (abdominal pain), upset stomach, constipation, loss of appetite, and too much water loss from the body (dehydration). These side effects are more common in patients age 80 and older.
- hand-and-foot syndrome (palms of the hands or soles of the feet tingle, become numb, painful, swollen or red), rash, dry, itchy or discolored skin, nail problems, and hair loss
- tiredness, weakness, dizziness, headache, fever, pain (including chest, back, joint, and muscle pain), trouble sleeping, and taste problems

These side effects may differ when taking XELODA with docetaxel (TAXOTERE). Please consult your doctor for possible side effects that may be caused by taking XELODA with docetaxel (TAXOTERE).

If you are concerned about these or any other side effects while taking XELODA, talk to your doctor.

Stop taking XELODA immediately and contact your doctor right away if you have the side effects listed below, or other side effects that concern you. Your doctor can then adjust XELODA to a dose that is right for you or stop your XELODA treatment for a while. This should help to reduce the side effects and stop them from getting worse.

- Diarrhea: if you have an additional 4 bowel movements each day beyond what is normal or any diarrhea at night
- Vomiting: if you vomit more than once in a 24-hour time period
- Nausea: if you lose your appetite, and the amount of food you eat each day is much less than usual
- Stomatitis: if you have pain, redness, swelling or sores in your mouth
- Hand-and-Foot Syndrome: if you have pain, swelling or redness of your hands or feet that prevents normal activity
- Fever or Infection: if you have a temperature of 100.5°F or greater, or other signs of infection

Your doctor may tell you to lower the dose or to stop XELODA treatment for a while. If caught early, most of these side effects usually improve after you stop taking XELODA. If they do not improve within 2 to 3 days, call your doctor again. After your side effects have improved, your doctor will tell you whether to start taking XELODA again and what dose to take. Adjusting the dose of XELODA to be right for each patient is an important part of treatment.

How should I store and use XELODA?

- Never share XELODA with anyone
- Store XELODA at normal room temperature (about 65° to 85°F)
- Keep XELODA and all other medicines out of the reach of children
- If you take too much XELODA by mistake, contact your doctor or local poison control center or emergency room right away

General advice about prescription medicines:

Medicines are sometimes prescribed for conditions that are not mentioned in patient information leaflets. Do not use XELODA for a condition for which it was not prescribed. Do not give XELODA to other people, even if they have the same symptoms you have. It may harm them.

This leaflet summarizes the most important information about XELODA. If you would like more information, talk with your doctor. You can ask your pharmacist or doctor for information about XELODA that is written for health professionals.

XELODA is a registered trademark of Hoffmann-La Roche Inc.

For full TAXOTERE prescribing information, please refer to TAXOTERE Package Insert.

Distributed by:

Genentech USA, Inc.
A Member of the Roche Group
1 DNA Way
South San Francisco, CA 94080-4990

XAT_091978_PI_2010_03(K)

Revised: February 2011

© 2011 Genentech, Inc. All rights reserved.

Relabeling and Repackaging by:
Physicians Total Care, Inc.
Tulsa, Oklahoma 74146

Representative sample of labeling (see the HOW SUPPLIED section for complete listing):

PRINCIPAL DISPLAY PANEL - 150 mg Tablet Bottle Label

Xeloda®
(capecitabine)
Tablets

150 mg

Each tablet contains 150 mg capecitabine.

Rx only

PRINCIPAL DISPLAY PANEL - 500 mg Tablet Bottle Label

Xeloda®
(capecitabine)
Tablets

500 mg

Each tablet contains
500 mg capecitabine.

Rx only